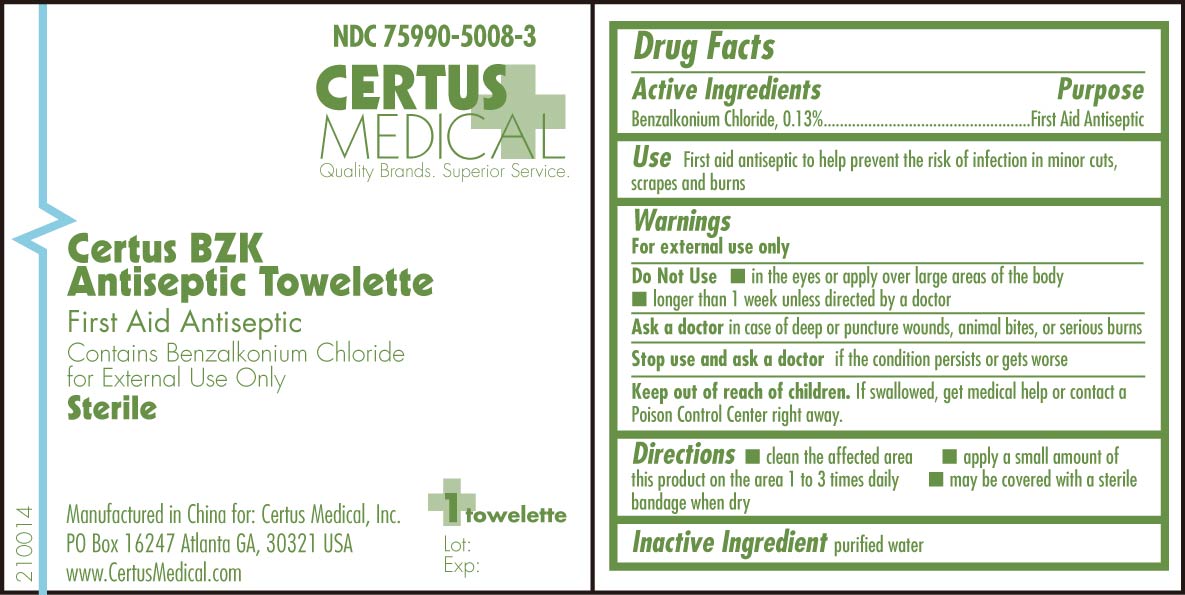 DRUG LABEL: Certus BZK Antiseptic Towelette
NDC: 75990-5008 | Form: SWAB
Manufacturer: Certus Medical, Inc.
Category: otc | Type: HUMAN OTC DRUG LABEL
Date: 20110412

ACTIVE INGREDIENTS: BENZALKONIUM CHLORIDE 0.0013 mL/1 mL
INACTIVE INGREDIENTS: WATER

Certus BZK Antiseptic Towelette 210014 Drug Facts and Label

Drug Facts Box OTC Active Ingredient Section

Benzalkonium Chloride 0.13%

Drug Facts Box OTC Purpose Section

First Aid Antiseptic

Drug Facts Box OTC Indications & Usage Section

First aid antiseptic to help prevent the risk of infection in minor cuts, scrapes and burns

Drug Facts Box OTC Warnings Section

For external use only

Drug Facts Box OTC Do Not Use Section

in the eyes or apply over large areas of the body

longer than 1 week unless directed by a doctor

Drug Facts Box OTC Ask Doctor Section

in case of deep or puncture wounds, animal bites, or serious burns

Drug Facts Box OTC Stop Use Section

and ask a doctor if the condition persists or gets worse

Drug Facts Box OTC Keep Out Of Reach Of Children Section

If swallowed, get medical help or contact a Poison Control Center right away.

Drug Facts Box OTC Dosage & Administration Section

clean the affected area

apply a small amount of this product on the area 1 to 3 times daily

may be covered with a sterile bandage when dry

Drug Facts Box OTC Inactive Ingredient Section

purified water

Certus BZK Antiseptic Towelette 210014 pouch

210014.jpg Certus BZK Antiseptic Towelette pouch